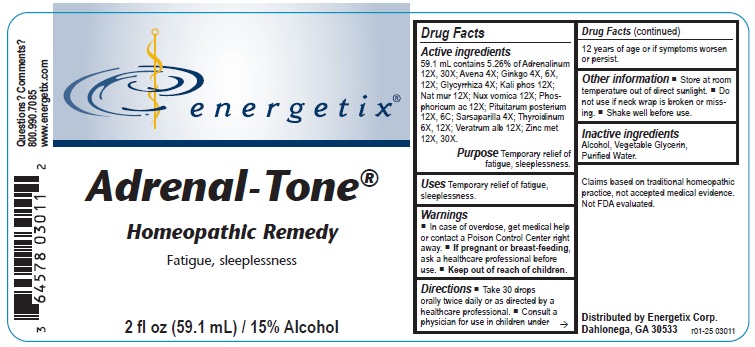 DRUG LABEL: Adrenal-Tone
NDC: 64578-0150 | Form: LIQUID
Manufacturer: Energetix Corporation
Category: homeopathic | Type: HUMAN OTC DRUG LABEL
Date: 20250711

ACTIVE INGREDIENTS: EPINEPHRINE 12 [hp_X]/59.1 mL; AVENA SATIVA FLOWERING TOP 4 [hp_X]/59.1 mL; GINKGO 4 [hp_X]/59.1 mL; GLYCYRRHIZA GLABRA 4 [hp_X]/59.1 mL; POTASSIUM PHOSPHATE, DIBASIC 12 [hp_X]/59.1 mL; SODIUM CHLORIDE 12 [hp_X]/59.1 mL; STRYCHNOS NUX-VOMICA SEED 12 [hp_X]/59.1 mL; PHOSPHORIC ACID 12 [hp_X]/59.1 mL; SUS SCROFA PITUITARY GLAND, POSTERIOR 12 [hp_X]/59.1 mL; SARSAPARILLA 4 [hp_X]/59.1 mL; THYROID, UNSPECIFIED 6 [hp_X]/59.1 mL; VERATRUM ALBUM ROOT 12 [hp_X]/59.1 mL; ZINC 12 [hp_X]/59.1 mL
INACTIVE INGREDIENTS: WATER; ALCOHOL; GLYCERIN

Adrenal-Tone

Active ingredients

59.1mL contains 5.26% of Adrenalinum 12X, 30X; Avena 4X; Ginkgo 4X, 6X, 12X; Glycyrrhiza 4X; Kali Phos 12X; Nat mur 12X; Nux vomica 12X; Phosphoricum ac 12X; Pituitarum posterium 12X 6C; Sarsaparilla 4X; Thyroidinum 6X, 12X; Veratrum alb 12X; Zinc Met 12X, 30X.

Claims based on traditional homeopathic practice, not accepted medical evidence. Not FDA evaluated.

Uses

Temporary relief of fatigue, sleeplessness.

Warnings

- In case of overdose, get medical help or contact a Poison Control Center right away.
- If pregnant or breast-feeding, ask a healthcare professional before use.

Keep out of reach of children.

Directions

- Take 30 drops orally twice daily or as directed by a healthcare professional.
- Consult a physician for use in children under 12 years of age or if symptoms worsen or persist.

Other information

- Store at room temperature out of direct sunlight.
- Do not use if neck wrap is broken or missing.
- Shake well before use.

Inactive ingredients

Alcohol, Vegetable Glycerin, Purified Water.

QUESTIONS

Distributed by Energetix Corp.

Dahlonega, GA 30533

Questions? Comments?

800-990-7085

www.energetix.com

PACKAGE LABEL

energetix

Adrenal-Tone

Homeopathic Remedy

Fatigue, sleeplessness

2 fl oz (59.1 mL) / 15% Alcohol

Purpose

Temporary relief of fatigue, sleeplessness.